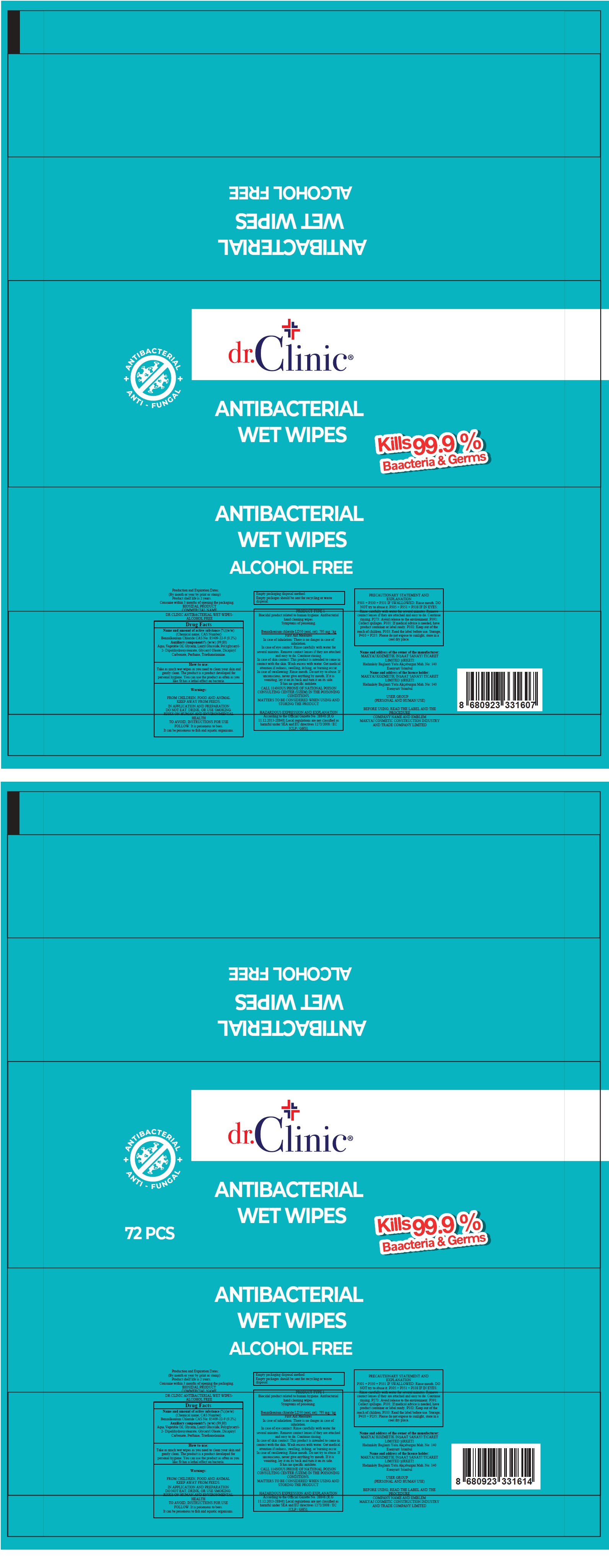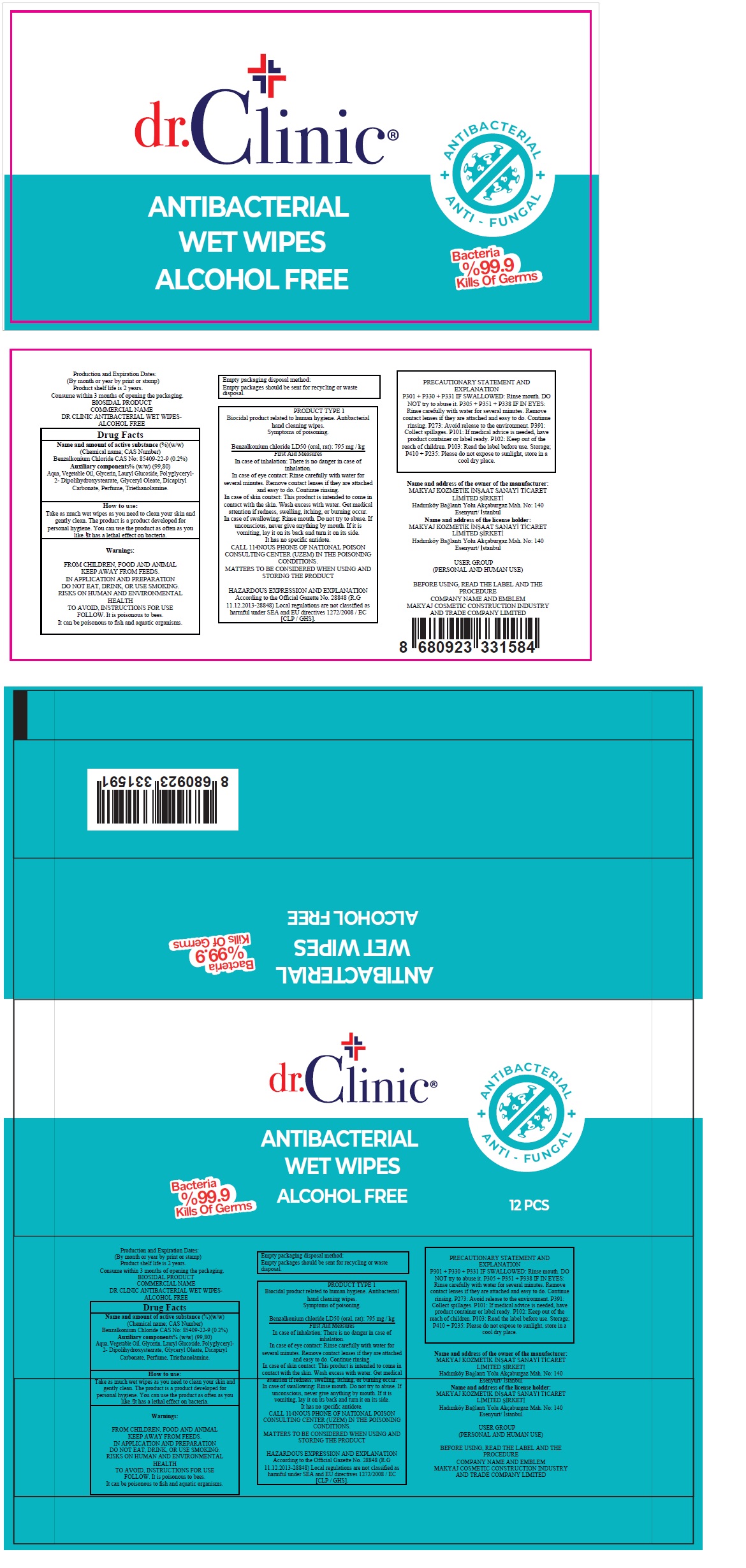 DRUG LABEL: dr.Clinic ANTIBACTERIAL WET WIPES ALCOHOL FREE
NDC: 76725-004 | Form: CLOTH
Manufacturer: MAKYAJ KOZMETIK INSAAT SANAYI VE TICARET LIMITED SIRKETI
Category: otc | Type: HUMAN OTC DRUG LABEL
Date: 20200601

ACTIVE INGREDIENTS: BENZALKONIUM CHLORIDE 0.2 g/100 g
INACTIVE INGREDIENTS: WATER; CORN OIL; GLYCERIN; LAURYL GLUCOSIDE; POLYGLYCERYL-2 DIPOLYHYDROXYSTEARATE; GLYCERYL OLEATE; DICAPRYLYL CARBONATE; TROLAMINE

dr.Clinic® ANTIBACTERIAL WET WIPES ALCOHOL FREE

Name and amount of active substance (%)(w/w)

(Chemical name; CAS Number)

Benzalkonium Chloride CAS No: 85409-22-9 (0.2%)

Purpose

Antibacterial

Uses:

- hand wipes to decrease bacteria on the skin
- recommended for repeated use
- for use when soap and water are not available

Warnings:

FROM CHILDREN, FOOD AND ANIMAL KEEP AWAY FROM FEEDS.
IN APPLICATION AND PREPARATION DO NOT EAT, DRINK, OR USE SMOKING.
RISKS ON HUMAN AND ENVIRONMENTAL HEALTH
TO AVOID, INSTRUCTIONS FOR USE FOLLOW. It is poisonous to bees.
It can be poisonous to fish and aquatic organisms.

Keep out of reach of children.

How to use:

Take as much wet wipes as you need to clean your skin and gently clean. The product is a product developed for personal hygiene. You can use the product as often as you like.! It has a lethal effect on bacteria.

Auxiliary components% (w/w)(99.80)

Aqua, Vegetable Oil, Glycerin, Lauryl Glucoside, Polyglyceryl-2- Dipolihydroxystearate, Glyceryl Oleate, Dicaprylyl Carbonate, Perfume, Triethanolamine.

ANTI - FUNGAL

Bacteria %99.9 Kills Of Germs

Product shelf life is 2 years.
Consume within 3 months of opening the packaging.
BIOSIDAL PRODUCT

Empty packaging disposal method:
Empty packages should be sent for recycling or waste disposal.

PRODUCT TYPE 1
Biocidal product related to human hygiene. Antibacterial hand cleaning wipes.
Symptoms of poisoning.

Benzalkonium chloride LD50 (oral, rat): 795 mg / kg
First Aid Measures
In case of inhalation: There is no danger in case of inhalation.
In case of eye contact: Rinse carefully with water for several minutes. Remove contact lenses if they are attached and easy to do. Continue rinsing.
In case of skin contact: This product is intended to come in contact with the skin. Wash excess with water. Get medical attention if redness, swelling, itching, or burning occur.
In case of swallowing: Rinse mouth. Do not try to abuse. If unconscious, never give anything by mouth. If it is vomiting, lay it on its back and turn it on its side.
It has no specific antidote.
CALL 114NOUS PHONE OF NATIONAL POISON CONSULTING CENTER (UZEM) IN THE POISONING CONDITIONS.
MATTERS TO BE CONSIDERED WHEN USING AND STORING THE PRODUCT

HAZARDOUS EXPRESSION AND EXPLANATION
According to the Official Gazette No. 28848 (R.G 11.12.2013-28848) Local regulations are not classified as harmful under SEA and EU directives 1272/2008 / EC [CLP / GHS].

PRECAUTIONARY STATEMENT AND EXPLANATION
P301 + P330 + P331 IF SWALLOWED: Rinse mouth. DO NOT try to abuse it. P305 + P351 + P338 IF IN EYES:
Rinse carefully with water for several minutes. Remove contact lenses if they are attached and easy to do. Continue rinsing. P273: Avoid release to the environment. P391: Collect spillages. P101: If medical advice is needed, have product container or label ready. P102: Keep out of the reach of children. P103: Read the label before use. Storage; P410 + P235: Please do not expose to sunlight, store in a cool dry place.

Name and address of the owner of the manufacturer:
MAKYAJ KOZMETIK INSAAT SANAYI TICARET LIMITED SIRKETI
Hadımköy Baglantı Yolu Akçaburgaz Mah. No: 140
Esenyurt/ Istanbul
Name and address of the license holder:
MAKYAJ KOZMETIK INSAAT SANAYI TICARET LIMITED SIRKETI
Hadımköy Baglantı Yolu Akçaburgaz Mah. No: 140
Esenyurt/ Istanbul

USER GROUP
(PERSONAL AND HUMAN USE)

BEFORE USING, READ THE LABEL AND THE PROCEDURE
COMPANY NAME AND EMBLEM
MAKYAJ COSMETIC CONSTRUCTION INDUSTRY AND TRADE COMPANY LIMITED